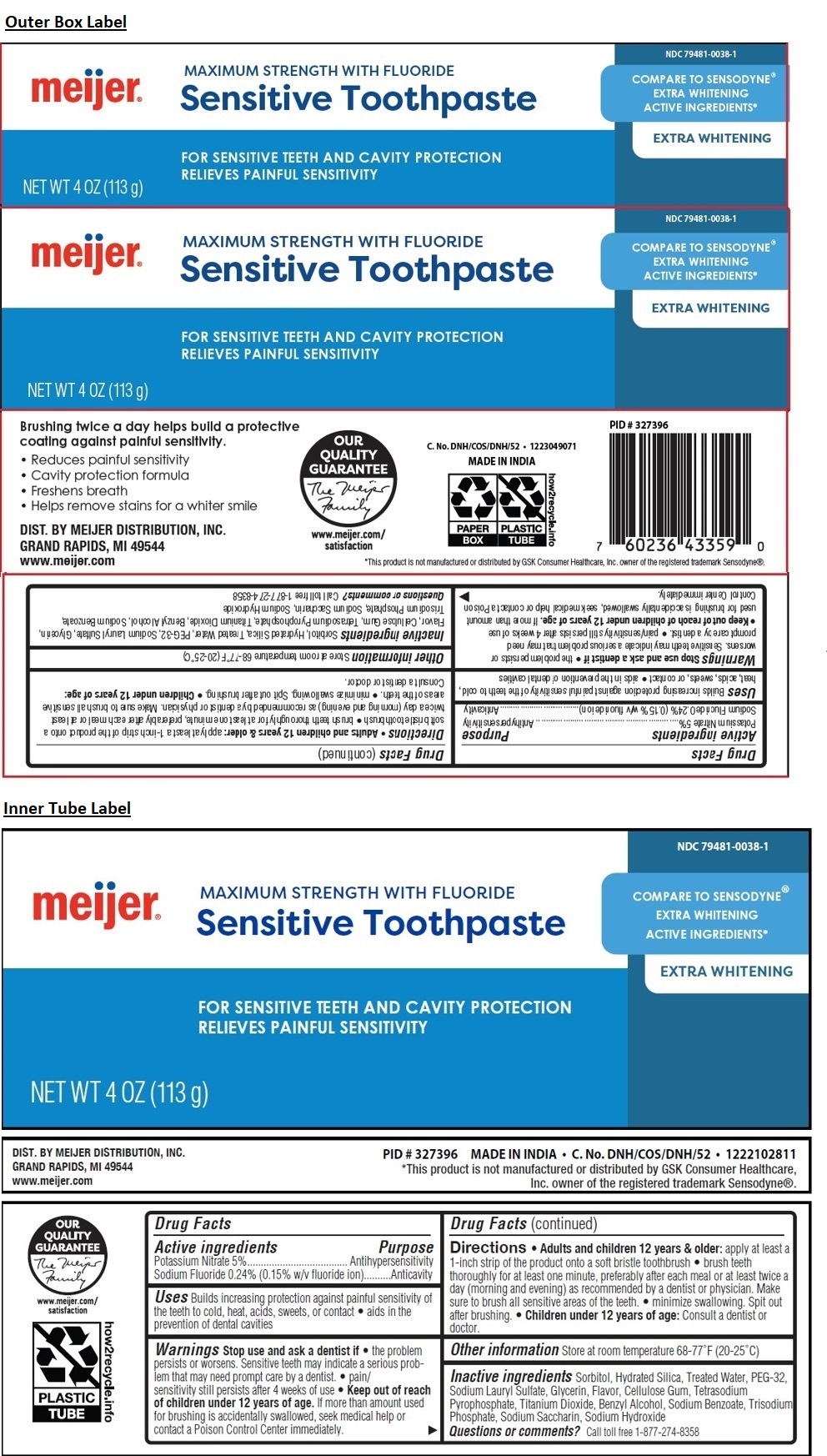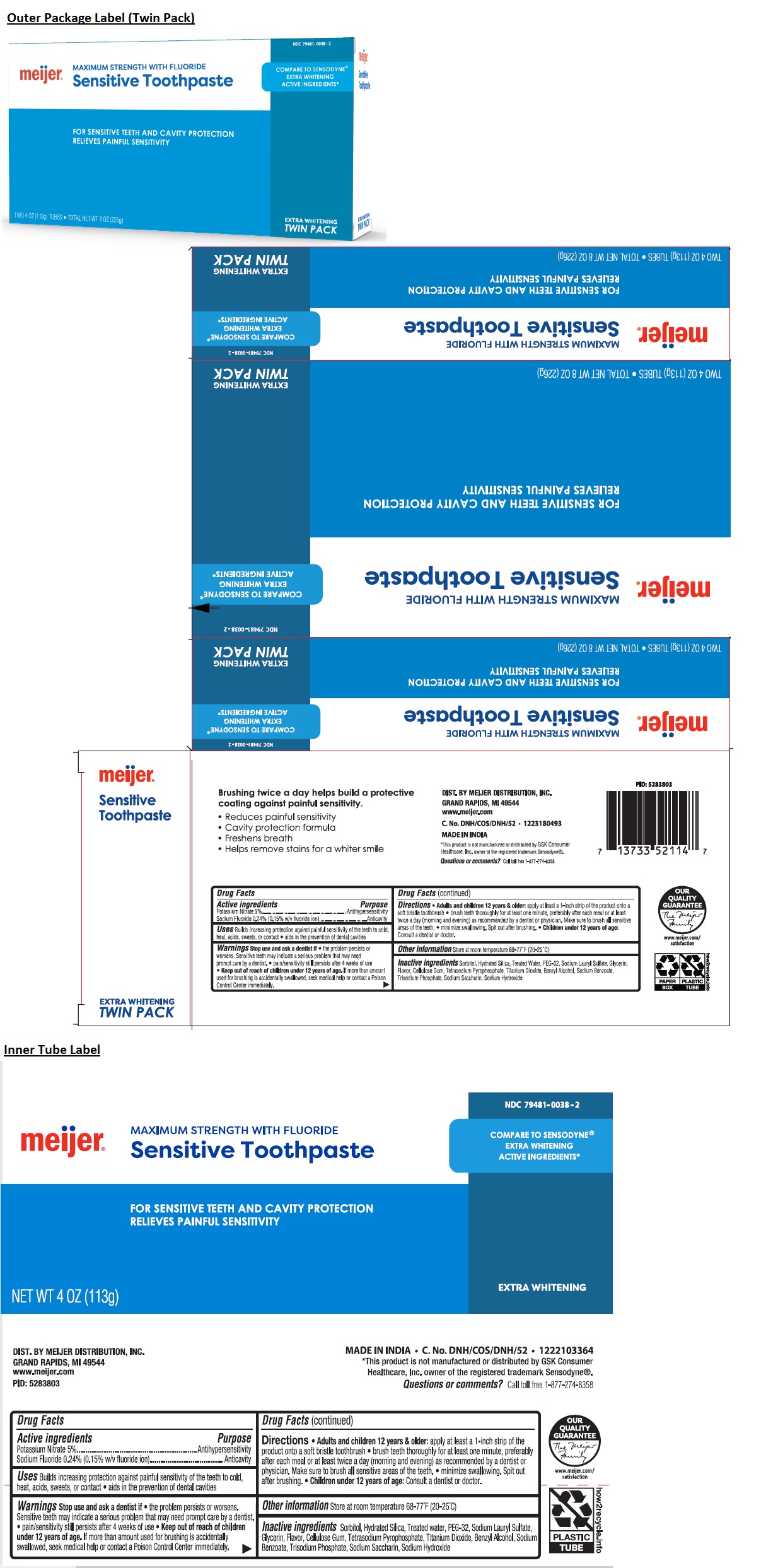 DRUG LABEL: meijer Sensitive EXTRA WHITENING
NDC: 79481-0038 | Form: PASTE, DENTIFRICE
Manufacturer: Meijer, Inc.
Category: otc | Type: HUMAN OTC DRUG LABEL
Date: 20251020

ACTIVE INGREDIENTS: POTASSIUM NITRATE 5 g/100 g; SODIUM FLUORIDE 0.24 g/100 g
INACTIVE INGREDIENTS: SORBITOL; HYDRATED SILICA; WATER; POLYETHYLENE GLYCOL 1600; SODIUM LAURYL SULFATE; GLYCERIN; CARBOXYMETHYLCELLULOSE SODIUM, UNSPECIFIED; SODIUM PYROPHOSPHATE; TITANIUM DIOXIDE; BENZYL ALCOHOL; SODIUM BENZOATE; SODIUM PHOSPHATE, TRIBASIC, ANHYDROUS; SACCHARIN SODIUM; SODIUM HYDROXIDE

meijer® Sensitive Toothpaste

Active ingredients

Potassium Nitrate 5%
Sodium Fluoride 0.24% (0.15% w/v fluoride ion)

Purpose

Antihypersensitivity
Anticavity

Uses

Builds increasing protection against painful sensitivity of the teeth to cold, heat, acids, sweets, or contact • aids in the prevention of dental cavities

Warnings

Stop use and ask a dentist if • the problem persists or worsens. Sensitive teeth may indicate a serious problem that may need prompt care by a dentist. • pain/sensitivity still persists after 4 weeks of use

• Keep out of reach of children under 12 years of age. If more than amount used for brushing is accidentally swallowed, seek medical help or contact a Poison Control Center immediately.

Directions

• Adults and children 12 years & older: apply at least a 1-inch strip of the product onto a soft bristle toothbrush • brush teeth thoroughly for at least one minute, preferably after each meal or at least twice a day (morning and evening) as recommended by a dentist or physician. Make sure to brush all sensitive areas of the teeth. • minimize swallowing. Spit out after brushing. • Children under 12 years of age: Consult a dentist or doctor.

Other information

Store at room temperature 68-77°F (20-25°C)

Inactive ingredients

Sorbitol, Hydrated Silica, Treated Water, PEG-32, Sodium Lauryl Sulfate, Glycerin, Flavor, Cellulose Gum, Tetrasodium Pyrophosphate, Titanium Dioxide, Benzyl Alcohol, Sodium Benzoate, Trisodium Phosphate, Sodium Saccharin, Sodium Hydroxide

Questions or comments?

Call toll free 1-877-274-8358

MAXIMUM STRENGTH WITH FLUORIDE

COMPARE TO SENSODYNE® EXTRA WHITENING ACTIVE INGREDIENTS*

FOR SENSITIVE TEETH AND CAVITY PROTECTION
RELIEVES PAINFUL SENSITIVITY

EXTRA WHITENING

TWIN PACK

Brushing twice a day helps build a protective coating against painful sensitivity.
• Reduces painful sensitivity
• Cavity protection formula
• Freshens breath
• Helps remove stains for a whiter smile

DIST. BY MEIJER DISTRIBUTION, INC.
GRAND RAPIDS, MI 49544
www.meijer.com

C. No. DNH/COS/DNH/52 • 1223049071 • 1223180493

MADE IN INDIA

*This product is not manufactured or distributed by GSK Consumer Healthcare, Inc. owner of the registered trademark Sensodyne®.

OUR QUALITY GUARANTEE
www.meijer.com/satisfaction